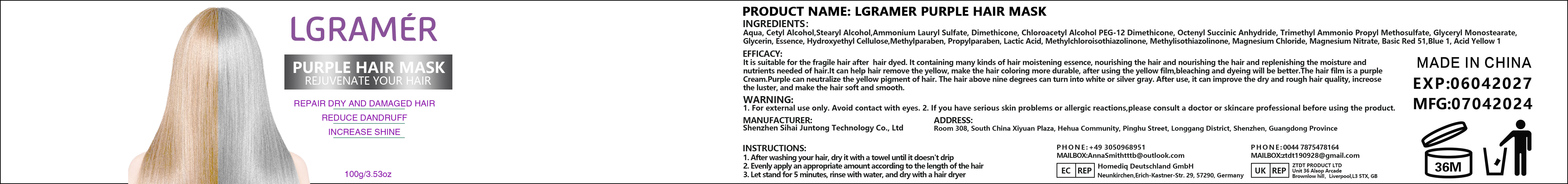 DRUG LABEL: LGRAMER PURPLE HAIR MASK
NDC: 84350-004 | Form: CREAM
Manufacturer: Shenzhen Sihai Juntong Technology Co., Ltd
Category: otc | Type: HUMAN OTC DRUG LABEL
Date: 20240813

ACTIVE INGREDIENTS: SQUALANE 1 g/100 mg
INACTIVE INGREDIENTS: WATER 1 g/100 mg

ACTIVE INGREDIENT

Glycerin 10%

INACTIVE INGREDIENT

Water 5%

PURPOSE

Moisturize

Warining

WARNING:1. For external use only. Avoid contact with eyes.2.lf you have serious skin problems or allergicreactions,please consult a doctor or skincareprofessional before using the product.

Do not use

If you have allergic reactions, stop to use

when using this product

1. After washing your hair, dry it with a towel until it doesn't drip2. Evenly apply an appropriate amount according to the length of the hair3. Let stand for 5 minutes, rinse with water, and dry with a hair dryer

Keep out of reach of children

use

INSTRUCTIONS:
1. After washing your hair, dry it with a towel until it doesn't drip
2. Evenly apply an appropriate amount according to the length of the hair
3. Let stand for 5 minutes, rinse with water, and dry with a hair dryer

Dosage and administration

appropriate amount

PRINCIPAL DISPLAY PANEL

100g NDC:84350-004-01